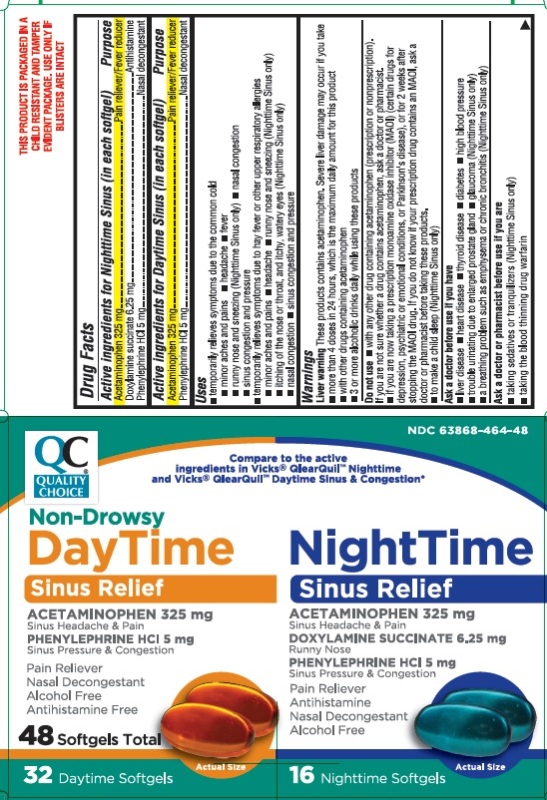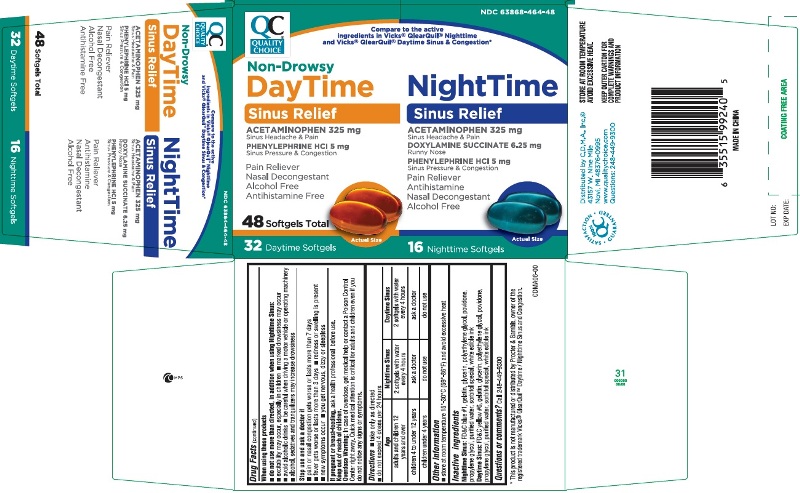 DRUG LABEL: Daytime Sinus Relief and Nighttime Sinus Relief
NDC: 63868-464 | Form: KIT | Route: ORAL
Manufacturer: Chain Drug Marketing Association Inc.
Category: otc | Type: HUMAN OTC DRUG LABEL
Date: 20191230

ACTIVE INGREDIENTS: ACETAMINOPHEN 325 mg/1 1; PHENYLEPHRINE HYDROCHLORIDE 5 mg/1 1; ACETAMINOPHEN 325 mg/1 1; PHENYLEPHRINE HYDROCHLORIDE 5 mg/1 1; DOXYLAMINE SUCCINATE 6.25 mg/1 1
INACTIVE INGREDIENTS: FD&C YELLOW NO. 6; GELATIN; GLYCERIN; POLYETHYLENE GLYCOL, UNSPECIFIED; POVIDONE; PROPYLENE GLYCOL; WATER; SORBITOL; FD&C BLUE NO. 1; GELATIN; GLYCERIN; POLYETHYLENE GLYCOL, UNSPECIFIED; POVIDONE; PROPYLENE GLYCOL; WATER; SORBITOL

Daytime Sinus Relief and Nighttime Sinus Relief

Active ingredients for Nighttime Sinus (in each softgel)

Acetaminophen 325 mg

Doxylamine succinate 6.25 mg

Phenylephrine HCl 5 mg

Active ingredients for Daytime Sinus (in each softgel)

Acetaminophen 325 mg
Phenylephrine hydrochloride 5 mg

Purposes

Nighttime Sinus Relief

Pain reliever/Fever reducer

Antihistamine

Nasal decongestant

Purposes

Daytime Sinus Relief

Pain reliever/Fever reducer

Nasal decongestant

Uses

- temporarily relieves symptoms due to the common cold
  - minor aches and pains
  - headache
  - fever
  - runny nose and sneezing (Nighttime only)
  - nasal congestion
  - sinus congestion & pressure
- temporarily relieves symptoms due to hay fever or other upper respiratory allergies
  - minor aches and pains
  - headache
  - runny nose and sneezing (Nighttime only)
  - itching of the nose or throat, and itchy, watery eyes (Nighttime only)
  - nasal congestion
  - sinus congestion & pressure

Warnings

Liver warning

These products contain acetaminophen. Severe liver damage may occur if you take

- more than 10 softgels in 24 hours, which is the maximum daily amount for this product
- with other drugs containing acetaminophen
- 3 or more alcoholic drinks every day while using this product

Do not use

- with any other drug containing acetaminophen (prescription or nonprescription). If you are not sure whether a drug contains acetaminophen, ask a doctor or pharmacist.
- if you are now taking a prescription monoamine oxidase inhibitor (MAOI) (certain drugs for depression, psychiatric or emotional conditions, or Parkinson's disease), or for 2 weeks after stopping the MAOI drug. If you do not know if your prescription drug contains an MAOI, ask a doctor or pharmacist before taking this product.
- to make a child sleep (Nighttime only)

Ask a doctor before use if you have

- liver disease
- heart disease
- thyroid disease
- diabetes
- high blood pressure
- glaucoma (Nighttime only)
- a breathing problem such as emphysema or chronic bronchitis (Nighttime only)
- trouble urinating due to enlarged prostate gland

Ask a doctor or pharmacist before use if you are

- taking sedatives or tranquilizers (Nighttime only)
- taking the blood thinning drug warfarin

When using this product

- do not use more than directed, in addition when using Nighttime Sinus and Congestion:
- excitability may occur, especially in children
- marked drowsiness may occur
- avoid alcoholic drinks
- be careful when driving a motor vehicle or operating machinery
- alcohol, sedatives & tranquilizers may increase drowsiness

Stop use and ask a doctor if

- pain or nasal congestion gets worse or last more than 7 days
- fever gets worse or lasts more than 3 days
- redness or swelling is present
- new symptoms occur
- you get nervous, dizzy or sleepless

PREGNANCY OR BREAST FEEDING

If pregnant or breast-feeding, ask a health professional before use.

Keep out of reach of children.

In case of overdose, get medical help or contact a Poison Control Center right away. Quick medical attention is critical for adults & for children even if you do not notice any signs or symptoms.

Directions

- take only as directed
- do not exceed 4 doses per 24 hours

Age | Daytime Sinus | Nighttime Sinus
adults and children 12 years and over | 2 softgels with water every 4 hours | 2 softgels with water every 4 hours
children 4 to under 12 years | ask a doctor | ask a doctor
children under 4 years | do not use | do not use

Other information

- store at room temperature 15°-30°C (59°-86°F) and avoid excessive heat

Inactive ingredients

Nighttime Sinus: FD&C blue #1, gelatin, glycerin, polyethylene glycol, povidone, propylene glycol, purified water, sorbitol special, white edible ink

Daytime Sinus: FD&C yellow #6, gelatin, glycerin, polyethylene glycol, povidone, propylene glycol, purified water, sorbitol special, white edible ink

Questions or comments?

Call 248-449-9300

Principal Display Panel

CDMA Daytime Sinus Relief and Nighttime Sinus Relief 48 SOFTGELS

NDC 63868-464-48

Compare to the active ingredients in Vicks® QlearQuilTM Daytime Sinus & Congestion and Nighttime Sinus & Congestion*